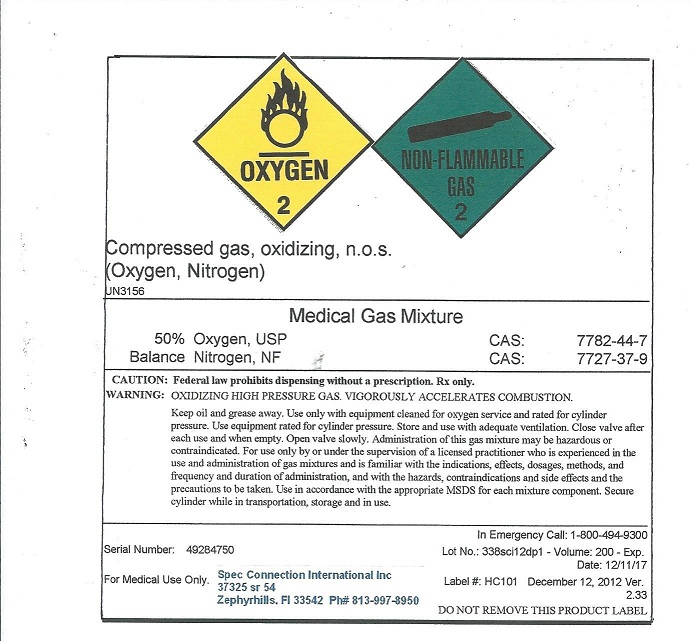 DRUG LABEL: Hyperbaric Chamber Mix
NDC: 54776-002 | Form: GAS
Manufacturer: Spec Connection International Inc
Category: prescription | Type: HUMAN PRESCRIPTION DRUG LABEL
Date: 20121227

ACTIVE INGREDIENTS: Oxygen 500 mL/1 L; Nitrogen 500 mL/1 L

Hyperbaric Chamber Mix

PACKAGE LABEL

OXYGEN 2 NON-FLAMMABLE GAS 2 Compressed gas, oxidizing, n.o.s. (Oxygen, Nitrogen) UN3156 Medical Gas Mixture 50% Oxygen, USP CAS: 7782-44-7 Balance Nitrogen, NF CAS: 7727-37-9 CAUTION: Federal law prohibits dispensing without a prescription. Rx only. WARNING: OXIDIZIN HIGH PRESSURE GAS. VIGOROUSLY ACCELERATES COMBUSTION. Keep oil and grease away. Use only with equipment cleaned for oxygen service and rated for cylinder pressure. Use equipment rated for cylinder pressure. Store and use with adequate ventilation. Close valve after each use and when empty. Open valve slowly. Administration of this gas mixture may be hazardous or contraindicated. For use only by or under the supervision of a licensed practitioner who is experienced in the use and administration of gas mixtures and is familiar with the indications, effects, dosages, methods, and frequency and duration of administration, and with the hazards, contraindications and side effects and the precautions to be taken. Use in accordance with the appropriate MSDS for each mixture component. Secure cylinder while in transportation, storage and in use. Serial Number: 49284750 In Emergency Call: 1-800-494-9300 Lot No.: 338sci12dp1 - Volume: 200 - Exp. Date: 12/11/17 Label #: HC101 December 12, 2012 Ver. 2.33 For Medical Use Only. Spec Connection International Inc 37325 sr 54 Zephyrhills FL 33542 Ph# 813-997-8950 DO NOT REMOVE THIS PRODUCT LABEL